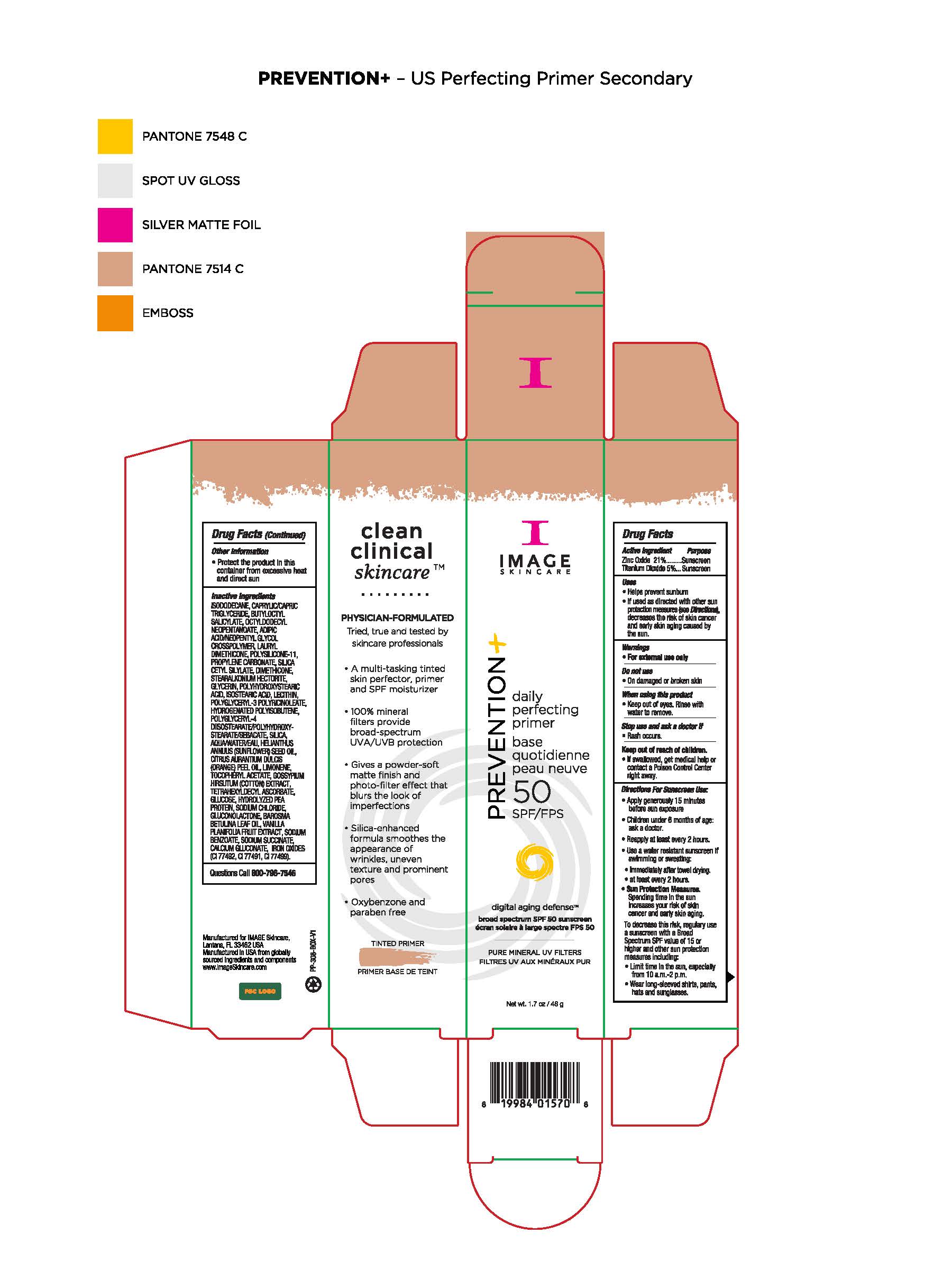 DRUG LABEL: Image Prevention Refiner Primer SPF50
NDC: 60232-1830 | Form: CREAM
Manufacturer: Swiss-American CDMO, LLC
Category: otc | Type: HUMAN OTC DRUG LABEL
Date: 20231106

ACTIVE INGREDIENTS: ZINC OXIDE 210 g/1000 g; TITANIUM DIOXIDE 50 g/1000 g
INACTIVE INGREDIENTS: ISODODECANE; BUTYLOCTYL SALICYLATE; OCTYLDODECYL NEOPENTANOATE; PROPYLENE CARBONATE; DIMETHICONE; STEARALKONIUM HECTORITE; GLYCERIN; POLYHYDROXYSTEARIC ACID (2300 MW); ISOSTEARIC ACID; LECITHIN, SOYBEAN; WATER; LIMONENE, (+)-; .ALPHA.-TOCOPHEROL ACETATE; TETRAHEXYLDECYL ASCORBATE; SODIUM CHLORIDE; GLUCONOLACTONE; SODIUM BENZOATE; CALCIUM GLUCONATE; MEDIUM-CHAIN TRIGLYCERIDES; DIMETHICONE/VINYL DIMETHICONE CROSSPOLYMER (SOFT PARTICLE); SILICON DIOXIDE; HYDROGENATED POLYBUTENE (1300 MW); SUNFLOWER OIL; ORANGE OIL; GOSSYPIUM HIRSUTUM WHOLE; ANHYDROUS DEXTROSE; AGATHOSMA BETULINA LEAF OIL; VANILLA BEAN; FERROSOFERRIC OXIDE; FERRIC OXIDE RED; FERRIC OXIDE YELLOW

Image Prevention Refiner Primer SPF50

Warnings

For external use only. Do not use on damaged or broken skin. When using this product keep out of eyes. Rinse with water to remove. Stop use and ask a doctor if rash occurs. If swallowed, get medical help or contact a Poison Control Center right away.

Keep out of Reach of Children

Active Ingredients

Zinc Oxide 21% Sunscreen

Titanium Dioxide 5% Sunscreen

Uses

Helps prevent sunburn. If used as directed with other sun protection measures (see Directions), decreases the risk of skin cancer and early skin aging caused by the sun.

Uses

Helps prevent sunburn. If used as directed with other sun protection measures (see Directions), decreases the risk of skin cancer and early skin aging caused by the sun.

Directions

Apply generously 15 minutes before sun exposure. Children under 6 months of age: ask a doctor. Reapply at least every 2 hours. Use a water resistant sunscreen if swimming or sweating. Immediately after towel drying. At least every 2 hours. Use a water resistant sunscreen when swimming or sweating, immediately after towel drying, at least every two hours. Sun Protection Measures. Spending time in the sun increases your risk of skin cancer and early skin aging. To decrease this risk, regularly use a sunscreen with a Broad Spectrum SPF value of 15 or higher and other sun protection measures including: limit time in the sun, especially from 10am to 2pm, wear long-sleeved shirts, pants, hats and sunglasses.

Other Information

Protect the product in this container from excessive heat and direct sun.

Inactive Ingredients

idododecane, caprylic/capric triglyceride, butyloctyl salicylate, octyldodecyl neopentanoate, adipic acid/neopentyl glycol crosspolymer, lauryl dimethicone, polysilicone-11, propylene carbonate, silica cetyl silylate, dimethicone, stearalkonium hectorite, glycerin, polyhydroxystearic acid, isostearic acid, lecithin, polyglyceryl-3 polyricinoleate, hydrogenated polyisobutene, polyglyceryl-4 diisotearate/polyhydroxystearate/sebacate, silica, water, helinathus annuus (sunflower) seed oil, citrus aurantium dulcis (orange) peel oil, limonene, tocopheryl acetate, gossypium hirsuthum (cotton) extract, tetrahexyldecyl ascorbate, glucose, hydrolyzed pea protein, sodium chloride, glyconolactone, barosma betulina leaf oil, vanilla planifolia fruit extract, sodium benzoate, sodium succinate, calcium glyconate, iron oxides (CI77492, CI77491, CI77499)

Questions

Questions Call 800-796-7546